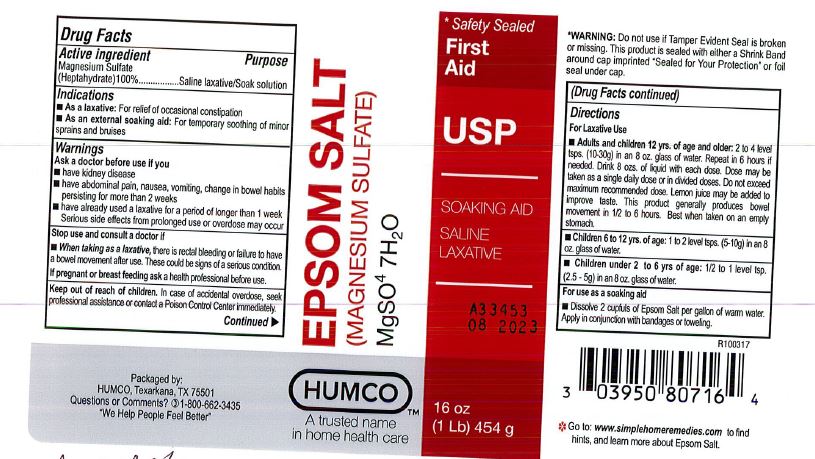 DRUG LABEL: Humco Epson Salt
NDC: 0395-0807 | Form: POWDER, FOR SOLUTION
Manufacturer: Humco Holding Group, Inc.
Category: otc | Type: HUMAN OTC DRUG LABEL
Date: 20231215

ACTIVE INGREDIENTS: MAGNESIUM SULFATE HEPTAHYDRATE 1000 mg/1 g
INACTIVE INGREDIENTS: WATER

Humco Epsom Salt USP

Drug Facts

Active ingredient

Magnesium Sulfate (heptahydrate) 100%

Puropose

Laxative/Soak solution

Use

As a laxative: For relief of occasional constipation.

As an external soaking aid: For temporary relief of minor sprains and bruises.

Warnings

Ask as a doctor before use if you:

haeve kidney disease or diabetes. Have abdominal pain, nausea, vomiting, change in bowel habits persisting more than 2 weeks. Have already used a laxative for a period longer than 1 week.

Serious side effects from prolonged use or overdose may occur.

Are taking prescription drugs.

Stop use and consult a doctor if

When taking as laxative, there is rectal bleeding or failure to have a bowel movement after use. These could be signs of a serious condition.

When using as soaking aid, discontinue use where promt relief is not obtained or where there is evidence of infection. Hot or warm soaks should not be used by individuals with diabetes except on the advice of a physician.

If pregnant or breasfeeding, ask a health professional before use.

Keep out of reach of children.

In case of accidental overdose, seek preofessional assistance or contact Poison Control Center immediately.

Directions

For laxative use. Adults and children 12 yrs. of age and older: 2 to 4 level tsps (10 - 30 g) in an 8 oz glass of water. Repeat in 6 hours if needed. Drink 8 ozs of liquid with each dose. limit 2 doses per day. Lemon juice may be added to improve taste. this product generally produces bowel movements in 1/2 to 6 hours. Best when taken on an empty stomach.

Children 6 to 12 yrs of age: Consulta doctor before use.

For use as a soaking aid: Dissolve 2 cupfuls of Epson Salt per gallon of warm water. apply in conjunction with bandages or toweling.

Inactive ingredient

None